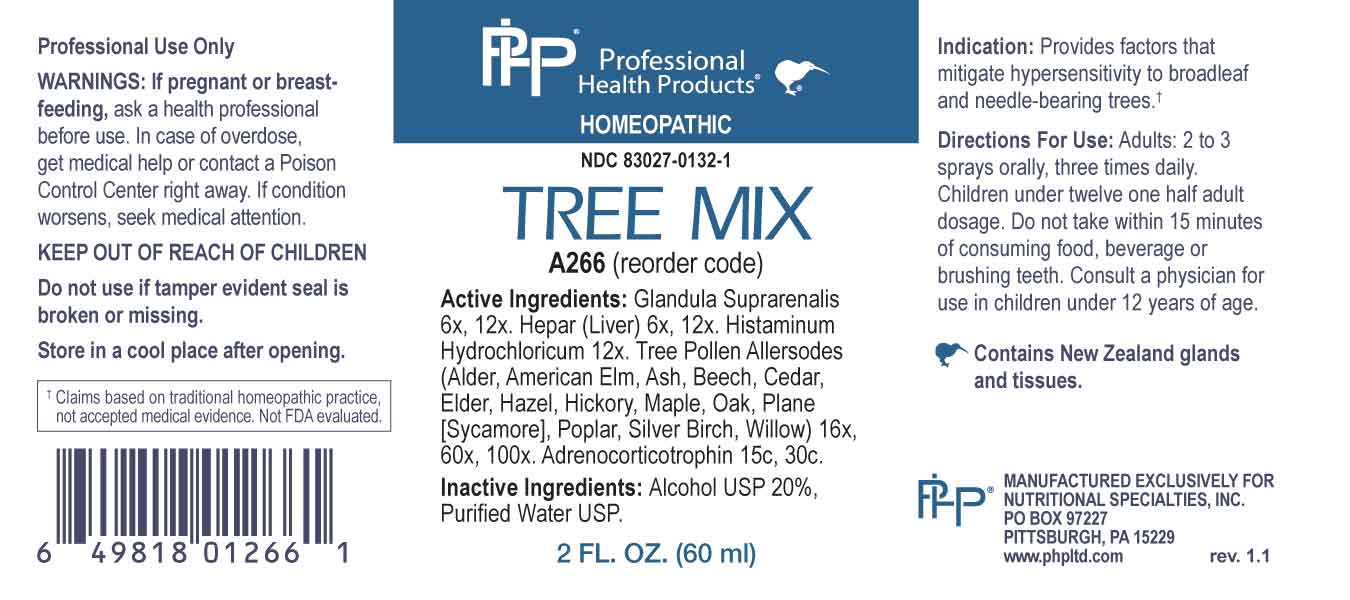 DRUG LABEL: Tree Mix
NDC: 83027-0132 | Form: SPRAY
Manufacturer: Nutritional Specialties, Inc.
Category: homeopathic | Type: HUMAN OTC DRUG LABEL
Date: 20240422

ACTIVE INGREDIENTS: BOS TAURUS ADRENAL GLAND 6 [hp_X]/1 mL; BEEF LIVER 6 [hp_X]/1 mL; HISTAMINE DIHYDROCHLORIDE 12 [hp_X]/1 mL; ALNUS RUBRA POLLEN 16 [hp_X]/1 mL; ULMUS AMERICANA POLLEN 16 [hp_X]/1 mL; FRAXINUS EXCELSIOR POLLEN 16 [hp_X]/1 mL; FAGUS SYLVATICA POLLEN 16 [hp_X]/1 mL; JUNIPERUS VIRGINIANA POLLEN 16 [hp_X]/1 mL; SAMBUCUS CANADENSIS FLOWER 16 [hp_X]/1 mL; CORYLUS AVELLANA POLLEN 16 [hp_X]/1 mL; CARYA GLABRA POLLEN 16 [hp_X]/1 mL; ACER SACCHARUM POLLEN 16 [hp_X]/1 mL; QUERCUS ROBUR POLLEN 16 [hp_X]/1 mL; PLATANUS X ACERIFOLIA POLLEN 16 [hp_X]/1 mL; POPULUS ALBA POLLEN 16 [hp_X]/1 mL; BETULA PENDULA POLLEN 16 [hp_X]/1 mL; SALIX X FRAGILIS POLLEN 16 [hp_X]/1 mL; CORTICOTROPIN 15 [hp_C]/1 mL
INACTIVE INGREDIENTS: WATER; ALCOHOL

DRUG FACTS:

ACTIVE INGREDIENTS:

Glandula Suprarenalis 6X, 12X , Hepar (Liver) 6X, 12X, Histaminum Hydrochloricum 12X, Alder 16X, 60X, 100, American Elm 16X, 60X, 100, Ash 16X, 60X, 100, Beech 16X, 60X, 100, Cedar 16X, 60X, 100, Elder 16X, 60X, 100, Hazel 16X, 60X, 100, Hickory 16X, 60X, 100, Maple 16X, 60X, 100, Oak 16X, 60X, 100, Plane (sycamore) 16X, 60X, 100, Poplar 16X, 60X, 100, Silver Birch 16X, 60X, 100, Willow 16X, 60X, 100, Adrenocorticotrophin 15C, 30C.

PURPOSE:

Provides factors that mitigate hypersensitivity to broadleaf and needle-bearing trees.†

†Claims based on traditional homeopathic practice, not accepted medical evidence. Not FDA evaluated.

WARNINGS:

Professional Use Only

If pregnant or breast-feeding, ask a health professional before use.

In case of overdose, get medical help or contact a Poison Control Center right away.

If condition worsens, seek medical attention.

KEEP OUT OF REACH OF CHILDREN

Do not use if tamper evident seal is broken or missing.

Store in a cool place after opening

KEEP OUT OF REACH OF CHILDREN:

In case of overdose, get medical help or contact a Poison Control Center right away.

DIRECTIONS:

Adults: 2 to 3 sprays orally, three times daily. Children under twelve one half adult dosage. Do not take within 15 minutes of consuming food, beverage or brushing teeth. Consult a physician for use in children under 12 years of age.

INDICATIONS

Provides factors that mitigate hypersensitivity to broadleaf and needle-bearing trees.†

†Claims based on traditional homeopathic practice, not accepted medical evidence. Not FDA evaluated.

INACTIVE INGREDIENTS:

Alcohol USP 20%, Purified Water USP.

QUESTIONS:

MANUFACTURED EXCLUSIVELY FOR

NUTRITIONAL SPECIALTIES, INC.

PO BOX 97227

PITTSBURG, PA 15229

www.phpltd.com

PACKAGE LABEL DISPLAY:

Professional

Health Products

HOMEOPATHIC

NDC 83027-0132-1

TREE MIX

2 FL. OZ (60 ml)